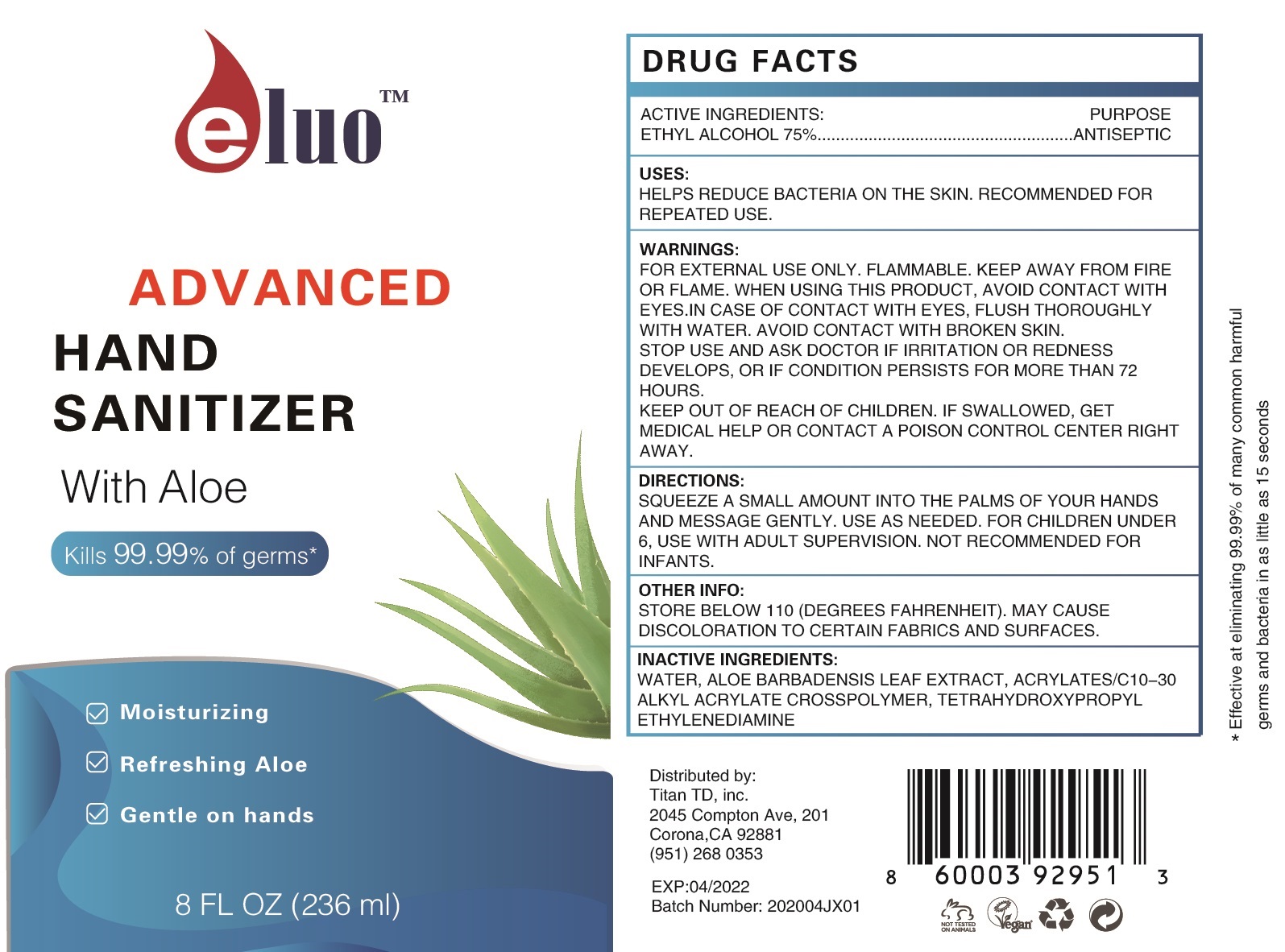 DRUG LABEL: Eluo Advanced Hand Sanitizer
NDC: 76869-008 | Form: GEL
Manufacturer: Titan Technology Distribution Inc dba Rixtan
Category: otc | Type: HUMAN OTC DRUG LABEL
Date: 20200509

ACTIVE INGREDIENTS: ALCOHOL 0.75 mL/1 mL
INACTIVE INGREDIENTS: WATER; ALOE VERA LEAF; CARBOMER INTERPOLYMER TYPE A (ALLYL SUCROSE CROSSLINKED); EDETOL

Eluo Advanced Hand Sanitizer

ACTIVE INGREDIENTS:

ETHYL ALCOHOL 75%

PURPOSE

ANTISEPTIC

USES:

HELPS REDUCE BACTERIA ON THE SKIN. RECOMMENDED FOR REPEATED USE.

WARNINGS:

FOR EXTERNAL USE ONLY. FLAMMABLE. KEEP AWAY FROM FIRE OR FLAME.

WHEN USING THIS PRODUCT,

AVOID CONTACT WITH EYES. IN CASE OF OCNTACT WITH EYES, FLUSH THOROUGHLY WITH WATER. AVOID CONTACT WITH BORKEN SKIN.

STOP USE AND ASK DOCTOR

IF IRRITATION OR REDNESS DEVELOPS, OR IF CONDITION PERSISTS FOR MORE THAN 72 HOURS.

KEEP OUT OF REACH OF CHILDREN.

IF SWALLOWED, GET MEDICAL HELP OR CONTACT A POISON CONTROL CENTER RIGHT AWAY.

DIRECTIONS:

SQUEEZE A SMALL AMOUNT INTO THE PALMS OF YOUR HANDS AND MASSAGE GENTLY. USE AS NEEDED. FOR CHILDREN UNDER 6, USE WITH ADULT SUPERVISION. NOT RECOMMENDED FOR INFANTS.

OTHER INFO:

STORE BELOW 110 (DEGREES FAHRENHEIT). MAY CAUSE DISCOLORATION TO CERTAIN FABRICS AND SURFACES.

INACTIVE INGREDIENTS

WATER, ALOE BARBADENSIS LEAF EXTRACT, ACRYLATES/C10-30 ALKYL ACRYLATE CROSSPOLYMER, TETRAHYDROXYPROPYL ETHYLENEDIAMNE